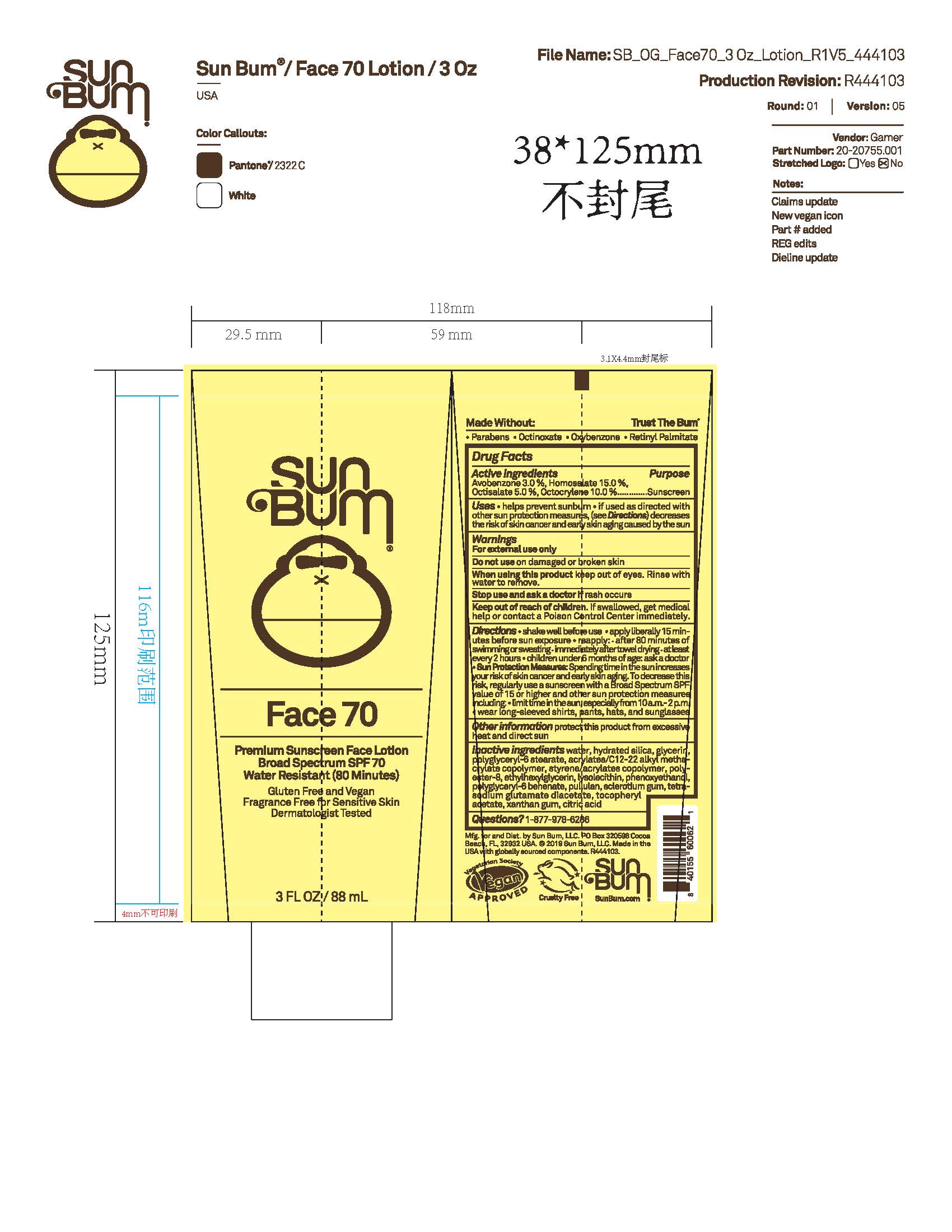 DRUG LABEL: Sun Bum Face 70 Premium Sunscreen
NDC: 69039-785 | Form: LOTION
Manufacturer: Sun Bum, LLC
Category: otc | Type: HUMAN OTC DRUG LABEL
Date: 20250811

ACTIVE INGREDIENTS: OCTOCRYLENE 100 mg/1 mL; AVOBENZONE 30 mg/1 mL; OCTISALATE 50 mg/1 mL; HOMOSALATE 150 mg/1 mL
INACTIVE INGREDIENTS: ETHYLHEXYLGLYCERIN; LUVISET 360; POLYGLYCERYL-6 BEHENATE; WATER; GLYCERIN; LYSOPHOSPHATIDYLCHOLINE, SOYBEAN; PHENOXYETHANOL; TETRASODIUM GLUTAMATE DIACETATE; .ALPHA.-TOCOPHEROL ACETATE; HYDRATED SILICA; XANTHAN GUM; CITRIC ACID; POLYGLYCERYL-6 STEARATE; ACRYLATES/C10-30 ALKYL ACRYLATE CROSSPOLYMER (60000 MPA.S); SCLEROTIUM GUM; POLYESTER-8 (1400 MW, CYANODIPHENYLPROPENOYL CAPPED); PULLULAN

Sun Bum Face 70 Premium Sunscreen

Active Ingredients

water, hydrated silica, glycerin, polyglyceryl-6 stearate, acrylates/C12-22 alkyl methacrylate copolymer, styrene/acrylates copolymer, polyester-8, ethylhexylglycerin, lysolecithin, phenoxyethanol, polyglyceryl-6 behenate, pullulan, sclerotium gum, tetrasodium glutamate diacetate, tocopheryl acetate, xanthan gum, citric acid

Purpose

Sunscreen

Uses

• helps prevent sunburn • if used as directed with other sun protection measures, (see Directions) decreases the risk of skin cancer and early skin aging caused by the sun

Warnings

For external use only

Do not use on damaged or broken skin

When using this product keep out of eyes. Rinse with water to remove.

Stop use and ask a doctor if rash occurs

Keep out of reach of children. If swallowed, get medical help or contact a Poison Control Center immediately.

Warnings

Keep Out Of Reach Of Children

Directions

• shake well before use

• apply liberally 15 minutes before sun exposure

• reapply: • after 80 minutes of swimming or sweating • immediately after towel drying • at least every 2 hours

• children under 6 months of age: ask a doctor

• Sun Protection Measures. Spending time in the sun increases your risk of skin cancer and early skin aging. To decrease this risk, regularly use a sunscreen with a Broad Spectrum SPF value of 15 or higher and other sun protection measures including:

• limit time in the sun, especially from 10 a.m.- 2 p.m.

• wear long-sleeved shirts, pants, hats and sunglasses

Directions

• shake well before use

• apply liberally 15 minutes before sun exposure

Other Information

protect this product from excessive heat and direct sun

Inactive Ingredients

water, hydrated silica, glycerin, polyglyceryl-6 stearate, acrylates/C12-22 alkyl methacrylate copolymer, styrene/acrylates copolymer, polyester-8, ethylhexylglycerin, lysolecithin, phenoxyethanol, polyglyceryl-6 behenate, pullulan, sclerotium gum, tetrasodium glutamate diacetate, tocopheryl acetate, xanthan gum, citric acid

Questions?

1-877-978-6286